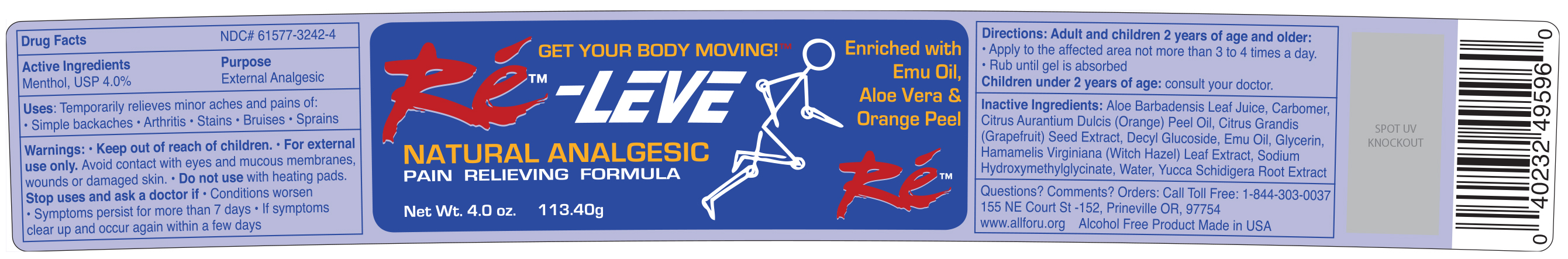 DRUG LABEL: RE-LEVE
NDC: 61577-3242 | Form: GEL
Manufacturer: SOMBRA COSMETICS INC.
Category: otc | Type: HUMAN OTC DRUG LABEL
Date: 20250529

ACTIVE INGREDIENTS: MENTHOL 0.06 g/1 g
INACTIVE INGREDIENTS: ALOE VERA LEAF; CARBOXYPOLYMETHYLENE; DECYL GLUCOSIDE; WATER; CITRUS MAXIMA SEED; GREEN TEA LEAF; FILIPENDULA ULMARIA FLOWER; ROSA DAMASCENA FLOWER OIL; SODIUM CARBONATE; GLYCERIN; HAMAMELIS VIRGINIANA LEAF; YUCCA SCHIDIGERA ROOT; LEMON OIL; PHENOXYETHANOL; CAPRYLYL GLYCOL

Ré-LEVE Natural Analgesic Pain Relieving Formula

Active Ingredients

Menthol USP 4%

Purpose

External Analgesic

Keep out of reach of children

Uses

Temporarily relieves minor aches and pains of muscles and joints associated with: simple backaches, strains, bruises, and sprains

Warnings

Keep out of reach of children. For external use only. Avoid contact with eyes and mucous membranes, wounds or damaged skin. Do not use with heating pads.

Stop uses and ask a doctor if: Conditions worsen, symptoms persist for more than 7 days, symptoms clear up and occur again within a few days.

Directions

Adult and children 2 years of age and older: apply to affected area not more than 3 to 4 times daily, rub until gel is absorbed, children under 2 years of age: consult your doctor.

Inactive Ingredients

aloe barbadensis leaf juice, carbomer, decyl glucoside, water, citrus grandis (grapefruit) seed extract, emu oil, citrus aurantium dulcis (orange) peel oil, glycerin, hamamelis virginiana (witch hazel) leaf extract, yucca schidigera root extract, sodium hydroxymethylglycinate

Questions or Comments? Orders:

Call toll-free: 1-844-303-0037, 155 NE Court St.-152, Prineville, OR, 97754. www.allforu.org. Alcohol-free product made in USA.